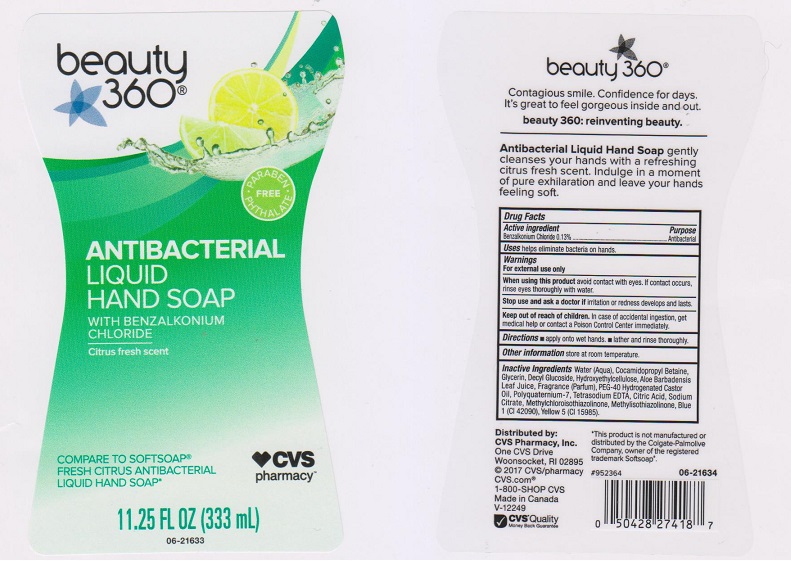 DRUG LABEL: CVS Pharmacy
NDC: 59779-724 | Form: LIQUID
Manufacturer: CVS Pharmacy
Category: otc | Type: HUMAN OTC DRUG LABEL
Date: 20170412

ACTIVE INGREDIENTS: BENZALKONIUM CHLORIDE 1.3 mg/1 mL
INACTIVE INGREDIENTS: WATER; COCAMIDOPROPYL BETAINE; GLYCERIN; DECYL GLUCOSIDE; HYDROXYETHYL CELLULOSE (5000 CPS AT 1%); ALOE VERA LEAF; POLYOXYL 40 HYDROGENATED CASTOR OIL; POLYQUATERNIUM-7 (70/30 ACRYLAMIDE/DADMAC; 1600000 MW); EDETATE SODIUM; CITRIC ACID MONOHYDRATE; SODIUM CITRATE; METHYLCHLOROISOTHIAZOLINONE; METHYLISOTHIAZOLINONE; FD&C BLUE NO. 1; FD&C YELLOW NO. 5

Active ingredient

Benzalkonium Chloride 0.13%

Purpose

Antibacterial

Uses

helps eliminate bacteria on hands.

Warnings

For external use only.

When using this product

avoid contact with eyes. If contact occurs, rinse eyes thoroughly with water.

Stop use and ask a doctor if

irritation or redness develops and lasts.

Keep out of reach of children.

In case of accidental ingestion, get medical help or contact a Poison Control Center immediately.

Directions

- apply onto wet hands.
- lather and rinse thoroughly.

Other information

store at room temperature.

Inactive ingredients

Water (Aqua), Cocamidopropyl Betaine, Glyceirn, Decyl Glucoside, Hydroxyethylcellulose, Aloe Barbadensis Leaf Juice, Fragrance (Parfum), PEG-40 Hydrogenated Castor Oil, Polyquaternium-7, Tetrasodium EDTA, Citric Acid, Sodium Citrate, Methylchloroisothiazolinone, Methylisothiazolinone, Blue 1 (CI 42090), Yellow 5 (CI 19140).